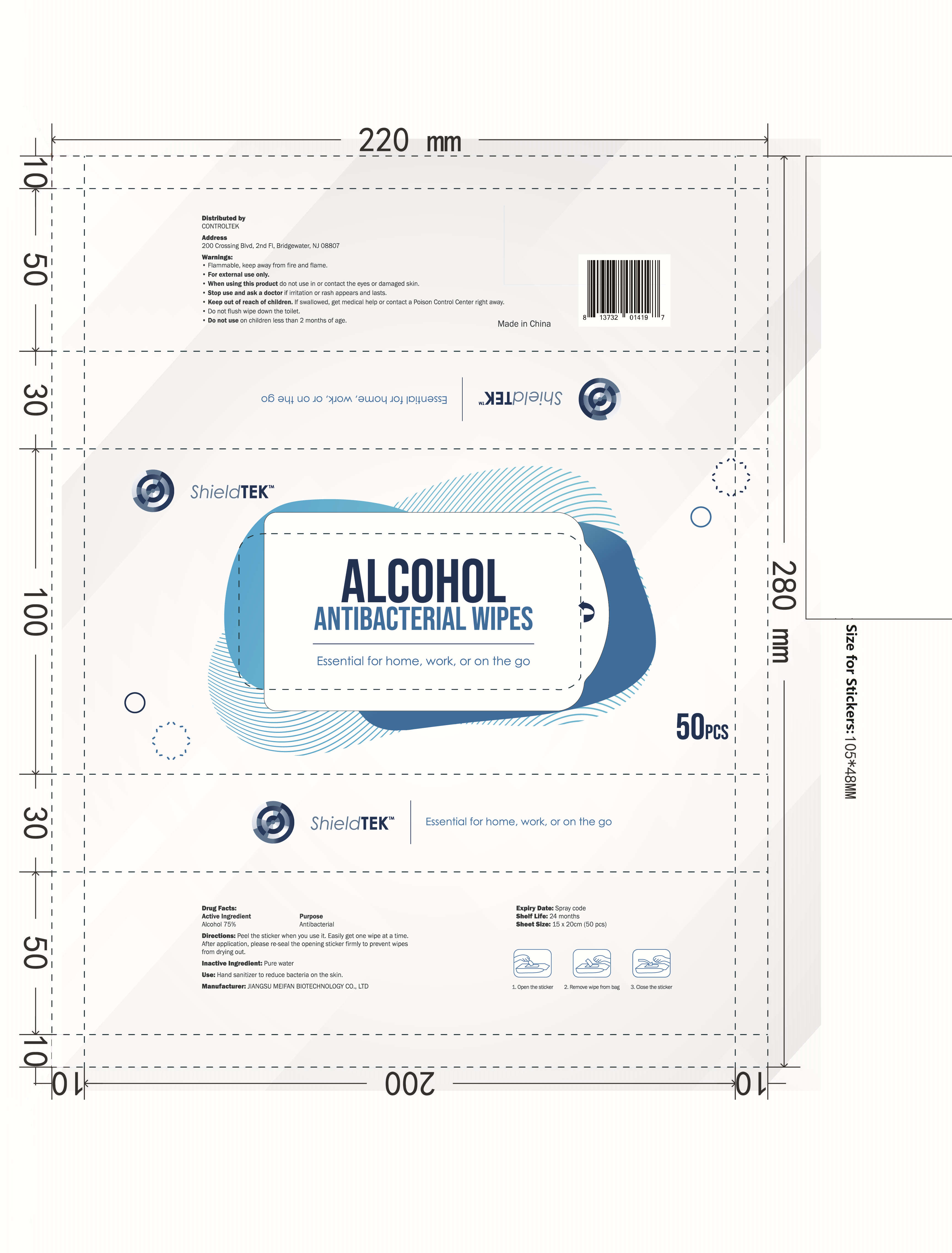 DRUG LABEL: ALCOHOL HAND WIPES
NDC: 55415-011 | Form: CLOTH
Manufacturer: JIANGSU MEIFAN BIOTECHNOLOGY CO., LTD.
Category: otc | Type: HUMAN OTC DRUG LABEL
Date: 20210205

ACTIVE INGREDIENTS: ALCOHOL 75 mL/100 mL
INACTIVE INGREDIENTS: WATER

DOSAGE AND ADMINISTRATION

Peel the sticker when you use it. Easily get one wipe at a time. After application, please re-seal the opening sticker firmly to prevent wipes from drying out.

INACTIVE INGREDIENT

Pure wate

INDICATIONS AND USAGE

Hand sanitizer to reduce bacteria on the skin.

ACTIVE INGREDIENT

Alcohol 75%

Keep out of reach of children. If swallowed, get medical help or contact a Poison Control Center right away.

Do not flush wipe down the toilet.

Do not use on children less than 2 months of age

PURPOSE

Hand sanitizer to reduce bacteria on the skin.

WARNINGS

Flammable, keep away from fire and flame.

For external use only.

When using this product, do not use in or contact the eyes or damaged skin.

Stop use and ask a doctor if irritation or rash appears and lasts.

STORAGE AND HANDLING

Store at room temperature in a cool, dry and ventilated place.